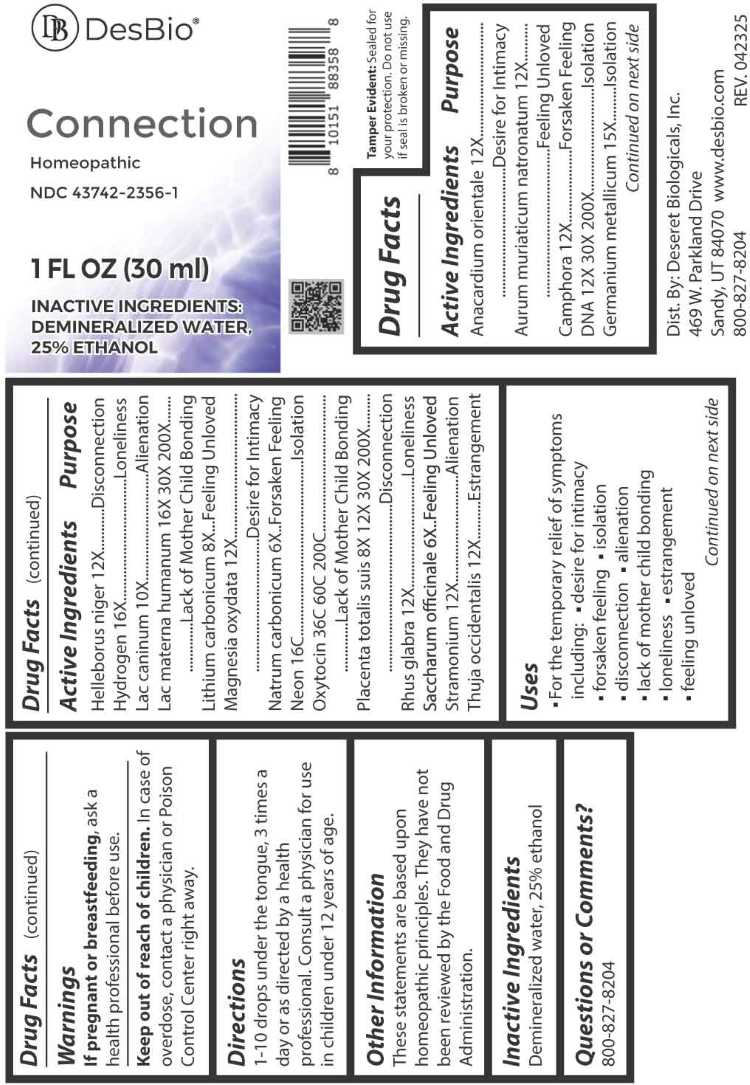 DRUG LABEL: Connection
NDC: 43742-2356 | Form: LIQUID
Manufacturer: Deseret Biologicals, Inc.
Category: homeopathic | Type: HUMAN OTC DRUG LABEL
Date: 20260219

ACTIVE INGREDIENTS: SEMECARPUS ANACARDIUM JUICE 12 [hp_X]/1 mL; SODIUM TETRACHLOROAURATE 12 [hp_X]/1 mL; CAMPHOR (NATURAL) 12 [hp_X]/1 mL; HERRING SPERM DNA 12 [hp_X]/1 mL; GERMANIUM 15 [hp_X]/1 mL; HELLEBORUS NIGER ROOT 12 [hp_X]/1 mL; HYDROGEN 16 [hp_X]/1 mL; CANIS LUPUS FAMILIARIS MILK 10 [hp_X]/1 mL; HUMAN MILK 16 [hp_X]/1 mL; LITHIUM CARBONATE 8 [hp_X]/1 mL; MAGNESIUM OXIDE 12 [hp_X]/1 mL; SODIUM CARBONATE 6 [hp_X]/1 mL; NEON 16 [hp_C]/1 mL; OXYTOCIN 36 [hp_C]/1 mL; SUS SCROFA PLACENTA 8 [hp_X]/1 mL; RHUS GLABRA TOP 12 [hp_X]/1 mL; SUCROSE 6 [hp_X]/1 mL; DATURA STRAMONIUM 12 [hp_X]/1 mL; THUJA OCCIDENTALIS LEAFY TWIG 12 [hp_X]/1 mL
INACTIVE INGREDIENTS: WATER; ALCOHOL

DRUG FACTS:

ACTIVE INGREDIENT:

Anacardium Orientale 12X, Aurum Muriaticum Natronatum 12X, Camphora 12X, DNA 12X, 30X, 200X, Germanium Metallicum 15X, Helleborus Niger 12X, Hydrogen 16X, Lac Caninum 10X, Lac Materna Humanum 16X, 30X, 200X, Lithium Carbonicum 8X, Magnesia Oxydata 12X, Natrum Carbonicum 6X, Neon 16C, Oxytocin 36C, 60C, 200C, Placenta Totalis Suis 8X, 12X, 30X, 200X, Rhus Glabra 12X, Saccharum Officinale 6X, Stramonium 12X, Thuja Occidentalis 12X.

PURPOSE:

Anacardium Orientale – Desire for Intimacy , Aurum Muriaticum Natronatum – Feeling Unloved, Camphora – Forsaken Feeling, DNA - Isolation, Germanium Metallicum - Isolation, Helleborus Niger - Disconnection, Hydrogen - Loneliness, Lac Caninum - Alienation, Lac Materna Humanum – Lack of Mother Child Bonding, Lithium Carbonicum – Feeling Unloved, Magnesia Oxydata – Desire for Intimacy, Natrum Carbonicum – Forsaken Feeling, Neon - Isolation, Oxytocin – Lack of Mother Child Bonding, Placenta Totalis Suis - Disconnection, Rhus Glabra - Loneliness, Saccharum Officinale – Feeling Unloved, Stramonium - Alienation, Thuja Occidentalis - Estrangement

USES:

• For the temporary relief of symptoms including:
• desire for intimacy • forsaken feeling • isolation • disconnection • alienation
• lack of mother child bonding • loneliness • estrangement • feeling unloved

These statements are based upon homeopathic principles. They have not been reviewed by the Food and Drug Administration.

WARNINGS:

If pregnant or breastfeeding, ask a health professional before use.

Keep out of reach of children. In case of overdose, contact a physician or Poison Control Center right away.

Tamper Evident: Sealed for your protection. Do not use if seal is broken or missing.

KEEP OUT OF REACH OF CHILDREN:

In case of overdose, contact a physician or Poison Control Center right away.

DIRECTIONS:

1-10 drops under the tongue, 3 times a day or as directed by a health professional.
Consult a physician for use in children under 12 years of age.

INACTIVE INGREDIENTS:

Demineralized water, 25% ethanol

QUESTIONS:

Dist. By: Deseret Biologicals, Inc.

469 W. Parkland Drive

Sandy, UT 84070

www.desbio.com

800-827-8204

PACKAGE LABEL DISPLAY:

DesBio

Connection

Homeopathic

NDC 43742-2356-1

1 FL OZ (30 ml)